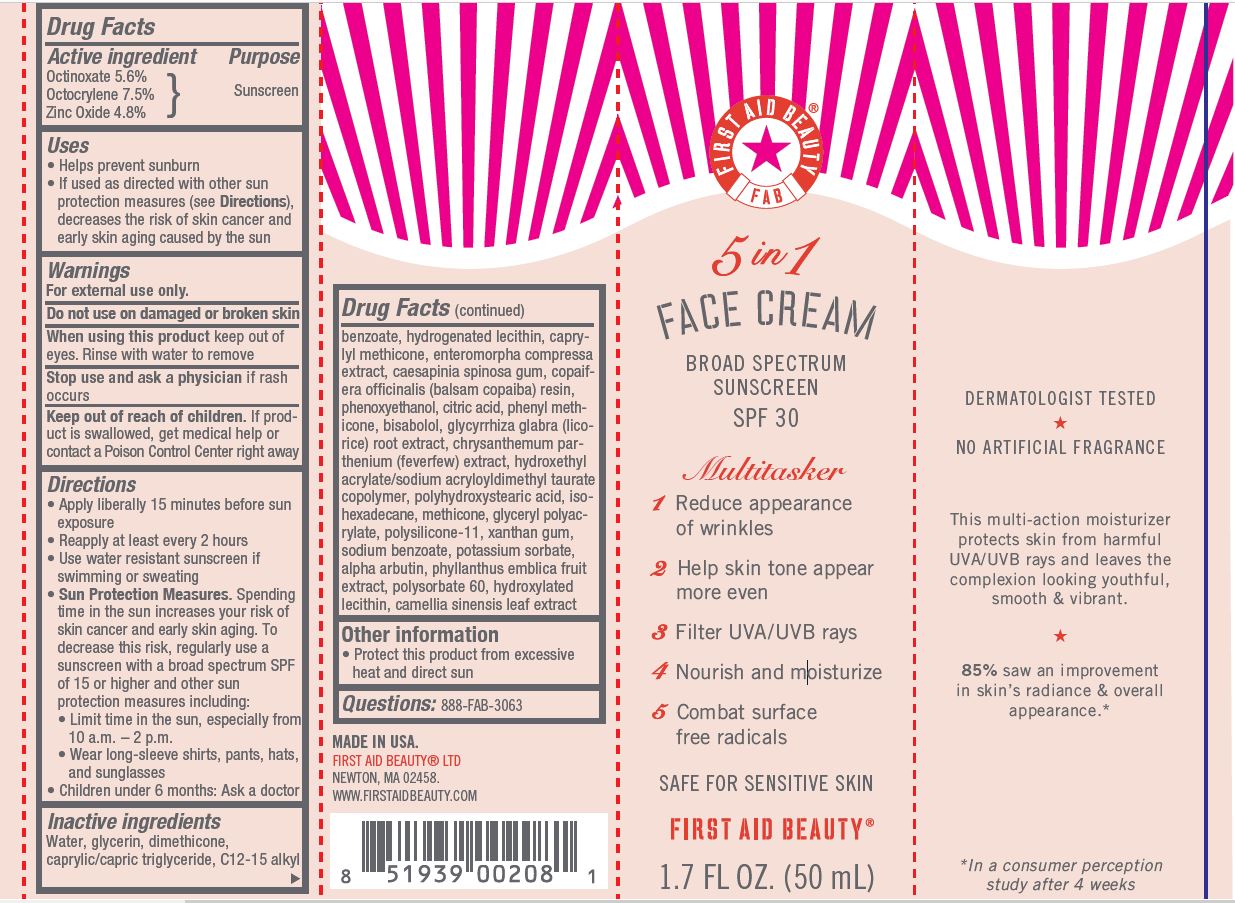 DRUG LABEL: First Aid Beauty FAB Broad Spectrum Sunscreen SPF 30
NDC: 69423-603 | Form: CREAM
Manufacturer: The Procter & Gamble Manufacturing Company
Category: otc | Type: HUMAN OTC DRUG LABEL
Date: 20251218

ACTIVE INGREDIENTS: OCTINOXATE 5.6 g/100 mL; OCTOCRYLENE 7.5 g/100 mL; ZINC OXIDE 4.8 g/100 mL
INACTIVE INGREDIENTS: DIMETHICONE/VINYL DIMETHICONE CROSSPOLYMER (SOFT PARTICLE); SODIUM BENZOATE; POTASSIUM SORBATE; XANTHAN GUM; WATER; ISOHEXADECANE; GLYCERIN; ALPHA-ARBUTIN; GREEN TEA LEAF; LEVOMENOL; ALKYL (C12-15) BENZOATE; CAESALPINIA SPINOSA RESIN; MEDIUM-CHAIN TRIGLYCERIDES; CAPRYLYL TRISILOXANE; TANACETUM PARTHENIUM; CITRIC ACID MONOHYDRATE; COPAIFERA OFFICINALIS RESIN; DIMETHICONE; ULVA COMPRESSA; GLYCYRRHIZA GLABRA; HYDROGENATED SOYBEAN LECITHIN; HYDROXYETHYL ACRYLATE/SODIUM ACRYLOYLDIMETHYL TAURATE COPOLYMER (100000 MPA.S AT 1.5%); METHICONE (20 CST); PHENOXYETHANOL; PHENYL METHICONE (500 CST); PHYLLANTHUS EMBLICA FRUIT; POLYHYDROXYSTEARIC ACID (2300 MW); POLYSORBATE 60

First Aid Beauty FAB Broad Spectrum Sunscreen SPF 30

Drug Facts

Active ingredients

Octinoxate 5.6%

Octocrylene 7.5%

Zinc oxide 4.8 %

PURPOSE

Sunscreen

Uses

- helps prevent sunburn
- if used as directed with other sun protection measures (see Directions), decreases the risk of skin cancer and early skin aging caused by the sun

Warnings

For external use only

Do not use

- on damaged or broken skin

When using this product

- keep out of eyes. Rinse with water to remove.

Stop use and ask a doctor if

- rash occurs

Keep out of reach of children. If product is swallowed, get medical help or contact a Poison Control Center right away.

Directions

- apply liberally 15 minutes before sun exposure
- reapply at least every 2 hours
- use water resistant sunscreen if swimming or sweating
- Sun Protection Measures. Spending time in the sun increases your risk of skin cancer and early skin aging. To decrease this risk, regularly use a sunscreen with a Broad Spectrum SPF value of 15 or higher and other sun protection measures including:
  - limit time in sun, especially from 10 a.m. - 2 p.m.
  - wear long-sleeved shirts, pants, hats, and sunglasses
- children under 6 months: ask a doctor

Other information

- protect this product from excessive heat and direct sun

Inactive ingredients

Water, glycerin, dimethicone, caprylic/capric triglyceride, C12-15 alkyl benzoate, hydrogenated lecithin, caprylyl methicone, enteromorpha compressa extract, caesapinia spinosa gum, copaifera officinalis (balsam copaiba) resin, phenoxyethanol, citric acid, phenyl methicone, bisabolol, glycyrrhiza glabra (licorice) root extract, chrysanthemum parthenium (feverfew) extract, hydroxethyl acrylate/sodium acryloyldimethyl taurate copolymer, polyhydroxystearic acid, isohexadecane, methicone, glyceryl polyacrylate, polysilicone-11, xanthan gum, sodium benzoate, potassium sorbate, alpha arbutin, phyllanthus emblica fruit extract, polysorbate 60, hydroxylated lecithin, camellia sinensis leaf extract

Questions?

888-FAB-3063

MADE IN USA.

FIRST AID BEAUTY ® LTD
NEWTON, MA 02458.

WWW.FIRSTAIDBEAUTY.COM

PACKAGE LABEL

First Aid Beauty

FAB

Broad Spectrum

Sunsceren

SPF 30

Muiltitasker

1 Reduce appearance of wrinkles

2 Help skin tone appear more even

3 Filter UVA/UVB rays

4 Nourish and moisturize

5 Combat surface free radicals

SAFE FOR SENSITIVE SKIN

FIRST AID BEAUTY ®

1.7 FL OZ (50 mL)